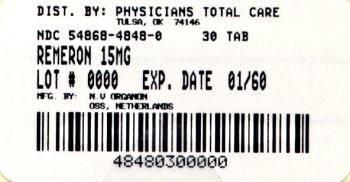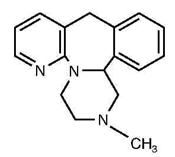 DRUG LABEL: REMERON
NDC: 54868-4498 | Form: TABLET, FILM COATED
Manufacturer: Physicians Total Care, Inc.
Category: prescription | Type: HUMAN PRESCRIPTION DRUG LABEL
Date: 20120217

ACTIVE INGREDIENTS: MIRTAZAPINE 30 mg/1 1
INACTIVE INGREDIENTS: STARCH, CORN; HYDROXYPROPYL CELLULOSE; MAGNESIUM STEARATE; SILICON DIOXIDE; LACTOSE

REMERON®
(mirtazapine)Tablets

Suicidality and Antidepressant Drugs

Antidepressants increased the risk compared to placebo of suicidal thinking and behavior (suicidality) in children, adolescents, and young adults in short-term studies of major depressive disorder (MDD) and other psychiatric disorders. Anyone considering the use of REMERON® (mirtazapine) Tablets or any other antidepressant in a child, adolescent, or young adult must balance this risk with the clinical need. Short-term studies did not show an increase in the risk of suicidality with antidepressants compared to placebo in adults beyond age 24; there was a reduction in risk with antidepressants compared to placebo in adults aged 65 and older. Depression and certain other psychiatric disorders are themselves associated with increases in the risk of suicide. Patients of all ages who are started on antidepressant therapy should be monitored appropriately and observed closely for clinical worsening, suicidality, or unusual changes in behavior. Families and caregivers should be advised of the need for close observation and communication with the prescriber. REMERON is not approved for use in pediatric patients. (See WARNINGS: Clinical Worsening and Suicide Risk, PRECAUTIONS: Information for Patients, and PRECAUTIONS: Pediatric Use)

DESCRIPTION

REMERON® (mirtazapine) Tablets are an orally administered drug. Mirtazapine has a tetra-cyclic chemical structure and belongs to the piperazino-azepine group of compounds. It is designated 1,2,3,4,10,14b-hexahydro-2-methylpyrazino [2,1-a] pyrido [2,3-c] benzazepine and has the empirical formula of C17H19N3. Its molecular weight is 265.36. The structural formula is the following and it is the racemic mixture:

Mirtazapine is a white to creamy white crystalline powder which is slightly soluble in water.

REMERON is supplied for oral administration as scored film-coated tablets containing 15 or 30 mg of mirtazapine, and unscored film-coated tablets containing 45 mg of mirtazapine. Each tablet also contains corn starch, hydroxypropyl cellulose, magnesium stearate, colloidal silicon dioxide, lactose, and other inactive ingredients.

CLINICAL PHARMACOLOGY

Pharmacodynamics

The mechanism of action of REMERON® (mirtazapine) Tablets, as with other drugs effective in the treatment of major depressive disorder, is unknown.

Evidence gathered in preclinical studies suggests that mirtazapine enhances central noradrenergic and serotonergic activity. These studies have shown that mirtazapine acts as an antagonist at central presynaptic α2 adrenergic inhibitory autoreceptors and heteroreceptors, an action that is postulated to result in an increase in central noradrenergic and serotonergic activity.

Mirtazapine is a potent antagonist of 5-HT2 and 5-HT3 receptors. Mirtazapine has no significant affinity for the 5-HT1A and 5-HT1B receptors.

Mirtazapine is a potent antagonist of histamine (H1) receptors, a property that may explain its prominent sedative effects.

Mirtazapine is a moderate peripheral α1 adrenergic antagonist, a property that may explain the occasional orthostatic hypotension reported in association with its use.

Mirtazapine is a moderate antagonist at muscarinic receptors, a property that may explain the relatively low incidence of anticholinergic side effects associated with its use.

Pharmacokinetics

REMERON (mirtazapine) Tablets are rapidly and completely absorbed following oral administration and have a half-life of about 20 to 40 hours. Peak plasma concentrations are reached within about 2 hours following an oral dose. The presence of food in the stomach has a minimal effect on both the rate and extent of absorption and does not require a dosage adjustment.

Mirtazapine is extensively metabolized after oral administration. Major pathways of biotransformation are demethylation and hydroxylation followed by glucuronide conjugation. In vitro data from human liver microsomes indicate that cytochrome 2D6 and 1A2 are involved in the formation of the 8-hydroxy metabolite of mirtazapine, whereas cytochrome 3A is considered to be responsible for the formation of the N-desmethyl and N-oxide metabolite. Mirtazapine has an absolute bioavailability of about 50%. It is eliminated predominantly via urine (75%) with 15% in feces. Several unconjugated metabolites possess pharmacological activity but are present in the plasma at very low levels. The (–) enantiomer has an elimination half-life that is approximately twice as long as the (+) enantiomer and therefore achieves plasma levels that are about 3 times as high as that of the (+) enantiomer.

Plasma levels are linearly related to dose over a dose range of 15 to 80 mg. The mean elimination half-life of mirtazapine after oral administration ranges from approximately 20 to 40 hours across age and gender subgroups, with females of all ages exhibiting significantly longer elimination half-lives than males (mean half-life of 37 hours for females vs. 26 hours for males). Steady state plasma levels of mirtazapine are attained within 5 days, with about 50% accumulation (accumulation ratio = 1.5).

Mirtazapine is approximately 85% bound to plasma proteins over a concentration range of 0.01 to 10 mcg/mL.

Special Populations

Geriatric

Following oral administration of REMERON (mirtazapine) Tablets 20 mg/day for 7 days to subjects of varying ages (range, 25–74), oral clearance of mirtazapine was reduced in the elderly compared to the younger subjects. The differences were most striking in males, with a 40% lower clearance in elderly males compared to younger males, while the clearance in elderly females was only 10% lower compared to younger females. Caution is indicated in administering REMERON to elderly patients (see PRECAUTIONS and DOSAGE AND ADMINISTRATION).

Pediatrics

Safety and effectiveness of mirtazapine in the pediatric population have not been established (see PRECAUTIONS).

Gender

The mean elimination half-life of mirtazapine after oral administration ranges from approximately 20 to 40 hours across age and gender subgroups, with females of all ages exhibiting significantly longer elimination half-lives than males (mean half-life of 37 hours for females vs. 26 hours for males) (see Pharmacokinetics).

Race

There have been no clinical studies to evaluate the effect of race on the pharmacokinetics of REMERON.

Renal Insufficiency

The disposition of mirtazapine was studied in patients with varying degrees of renal function. Elimination of mirtazapine is correlated with creatinine clearance. Total body clearance of mirtazapine was reduced approximately 30% in patients with moderate (Clcr = 11–39 mL/min/1.73 m^2) and approximately 50% in patients with severe (Clcr = <10 mL/min/1.73 m^2) renal impairment when compared to normal subjects. Caution is indicated in administering REMERON to patients with compromised renal function (see PRECAUTIONS and DOSAGE AND ADMINISTRATION).

Hepatic Insufficiency

Following a single 15-mg oral dose of REMERON, the oral clearance of mirtazapine was decreased by approximately 30% in hepatically impaired patients compared to subjects with normal hepatic function. Caution is indicated in administering REMERON to patients with compromised hepatic function (see PRECAUTIONS and DOSAGE AND ADMINISTRATION).

Clinical Trials Showing Effectiveness

The efficacy of REMERON (mirtazapine) Tablets as a treatment for major depressive disorder was established in 4 placebo-controlled, 6-week trials in adult outpatients meeting DSM-III criteria for major depressive disorder. Patients were titrated with mirtazapine from a dose range of 5 mg up to 35 mg/day. Overall, these studies demonstrated mirtazapine to be superior to placebo on at least 3 of the following 4 measures: 21-Item Hamilton Depression Rating Scale (HDRS) total score; HDRS Depressed Mood Item; CGI Severity score; and Montgomery and Asberg Depression Rating Scale (MADRS). Superiority of mirtazapine over placebo was also found for certain factors of the HDRS, including anxiety/somatization factor and sleep disturbance factor. The mean mirtazapine dose for patients who completed these 4 studies ranged from 21 to 32 mg/day. A fifth study of similar design utilized a higher dose (up to 50 mg) per day and also showed effectiveness.

Examination of age and gender subsets of the population did not reveal any differential responsiveness on the basis of these subgroupings.

In a longer-term study, patients meeting (DSM-IV) criteria for major depressive disorder who had responded during an initial 8 to 12 weeks of acute treatment on REMERON were randomized to continuation of REMERON or placebo for up to 40 weeks of observation for relapse. Response during the open phase was defined as having achieved a HAM-D 17 total score of ≤8 and a CGI-Improvement score of 1 or 2 at 2 consecutive visits beginning with week 6 of the 8 to 12 weeks in the open-label phase of the study. Relapse during the double-blind phase was determined by the individual investigators. Patients receiving continued REMERON treatment experienced significantly lower relapse rates over the subsequent 40 weeks compared to those receiving placebo. This pattern was demonstrated in both male and female patients.

INDICATIONS AND USAGE

REMERON® (mirtazapine) Tablets are indicated for the treatment of major depressive disorder.

The efficacy of REMERON in the treatment of major depressive disorder was established in 6-week controlled trials of outpatients whose diagnoses corresponded most closely to the Diagnostic and Statistical Manual of Mental Disorders – 3rd edition (DSM-III) category of major depressive disorder (see CLINICAL PHARMACOLOGY).

A major depressive episode (DSM-IV) implies a prominent and relatively persistent (nearly every day for at least 2 weeks) depressed or dysphoric mood that usually interferes with daily functioning, and includes at least 5 of the following 9 symptoms: depressed mood, loss of interest in usual activities, significant change in weight and/or appetite, insomnia or hypersomnia, psychomotor agitation or retardation, increased fatigue, feelings of guilt or worthlessness, slowed thinking or impaired concentration, a suicide attempt, or suicidal ideation.

The effectiveness of REMERON in hospitalized depressed patients has not been adequately studied.

The efficacy of REMERON in maintaining a response in patients with major depressive disorder for up to 40 weeks following 8 to 12 weeks of initial open-label treatment was demonstrated in a placebo-controlled trial. Nevertheless, the physician who elects to use REMERON for extended periods should periodically re-evaluate the long-term usefulness of the drug for the individual patient (see CLINICAL PHARMACOLOGY).

CONTRAINDICATIONS

Hypersensitivity

REMERON® (mirtazapine) Tablets are contraindicated in patients with a known hypersensitivity to mirtazapine or to any of the excipients.

Monoamine Oxidase Inhibitors

The concomitant use of REMERON Tablets and a monoamine oxidase (MAO) inhibitor is contraindicated. REMERON should not be used within 14 days of initiating or discontinuing therapy with a monoamine oxidase inhibitor (MAOI) (see WARNINGS, PRECAUTIONS, DRUG INTERACTIONS, and DOSAGE AND ADMINISTRATION).

WARNINGS

Clinical Worsening and Suicide Risk

Patients with major depressive disorder (MDD), both adult and pediatric, may experience worsening of their depression and/or the emergence of suicidal ideation and behavior (suicidality) or unusual changes in behavior, whether or not they are taking antidepressant medications, and this risk may persist until significant remission occurs. Suicide is a known risk of depression and certain other psychiatric disorders, and these disorders themselves are the strongest predictors of suicide. There has been a long-standing concern, however, that antidepressants may have a role in inducing worsening of depression and the emergence of suicidality in certain patients during the early phases of treatment. Pooled analyses of short-term placebo-controlled trials of antidepressant drugs (SSRIs and others) showed that these drugs increase the risk of suicidal thinking and behavior (suicidality) in children, adolescents, and young adults (ages 18–24) with major depressive disorder (MDD) and other psychiatric disorders. Short-term studies did not show an increase in the risk of suicidality with antidepressants compared to placebo in adults beyond age 24; there was a reduction in risk with antidepressants compared to placebo in adults aged 65 and older.

The pooled analyses of placebo-controlled trials in children and adolescents with MDD, obsessive compulsive disorder (OCD), or other psychiatric disorders included a total of 24 short-term trials of 9 antidepressant drugs in over 4400 patients. The pooled analyses of placebo-controlled trials in adults with MDD or other psychiatric disorders included a total of 295 short-term trials (median duration of 2 months) of 11 antidepressant drugs in over 77,000 patients. There was considerable variation in risk of suicidality among drugs, but a tendency toward an increase in the younger patients for almost all drugs studied. There were differences in absolute risk of suicidality across different indications, with the highest incidence in MDD. The risk differences (drug vs. placebo), however, were relatively stable within age strata and across indications. These risk differences (drug-placebo difference in the number of cases of suicidality per 1000 patients treated) are provided in Table 1.

Table 1
Age Range | Drug-Placebo Difference in Number of Cases of Suicidality per 1000 Patients Treated
Increases Compared to Placebo
<18 | 14 additional cases
18–24 | 5 additional cases
Decreases Compared to Placebo
25–64 | 1 fewer case
≥65 | 6 fewer cases

No suicides occurred in any of the pediatric trials. There were suicides in the adult trials, but the number was not sufficient to reach any conclusion about drug effect on suicide.

It is unknown whether the suicidality risk extends to longer-term use, i.e., beyond several months. However, there is substantial evidence from placebo-controlled maintenance trials in adults with depression that the use of antidepressants can delay the recurrence of depression.

All patients being treated with antidepressants for any indication should be monitored appropriately and observed closely for clinical worsening, suicidality, and unusual changes in behavior, especially during the initial few months of a course of drug therapy, or at times of dose changes, either increases or decreases.

The following symptoms, anxiety, agitation, panic attacks, insomnia, irritability, hostility, aggressiveness, impulsivity, akathisia (psychomotor restlessness), hypomania, and mania, have been reported in adult and pediatric patients being treated with antidepressants for major depressive disorder as well as for other indications, both psychiatric and nonpsychiatric. Although a causal link between the emergence of such symptoms and either the worsening of depression and/or the emergence of suicidal impulses has not been established, there is concern that such symptoms may represent precursors to emerging suicidality.

Consideration should be given to changing the therapeutic regimen, including possibly discontinuing the medication, in patients whose depression is persistently worse, or who are experiencing emergent suicidality or symptoms that might be precursors to worsening depression or suicidality, especially if these symptoms are severe, abrupt in onset, or were not part of the patient's presenting symptoms.

Families and caregivers of patients being treated with antidepressants for major depressive disorder or other indications, both psychiatric and nonpsychiatric, should be alerted about the need to monitor patients for the emergence of agitation, irritability, unusual changes in behavior, and the other symptoms described above, as well as the emergence of suicidality, and to report such symptoms immediately to health care providers. Such monitoring should include daily observation by families and caregivers. Prescriptions for REMERON® (mirtazapine) Tablets should be written for the smallest quantity of tablets consistent with good patient management, in order to reduce the risk of overdose.

Screening Patients for Bipolar Disorder

A major depressive episode may be the initial presentation of bipolar disorder. It is generally believed (though not established in controlled trials) that treating such an episode with an antidepressant alone may increase the likelihood of precipitation of a mixed/manic episode in patients at risk for bipolar disorder. Whether any of the symptoms described above represent such a conversion is unknown. However, prior to initiating treatment with an antidepressant, patients with depressive symptoms should be adequately screened to determine if they are at risk for bipolar disorder; such screening should include a detailed psychiatric history, including a family history of suicide, bipolar disorder, and depression. It should be noted that REMERON (mirtazapine) Tablets are not approved for use in treating bipolar depression.

Agranulocytosis

In premarketing clinical trials, 2 (1 with Sjögren's Syndrome) out of 2796 patients treated with REMERON (mirtazapine) Tablets developed agranulocytosis [absolute neutrophil count (ANC) <500/mm^3 with associated signs and symptoms, e.g., fever, infection, etc.] and a third patient developed severe neutropenia (ANC <500/mm^3 without any associated symptoms). For these 3 patients, onset of severe neutropenia was detected on days 61, 9, and 14 of treatment, respectively. All 3 patients recovered after REMERON was stopped. These 3 cases yield a crude incidence of severe neutropenia (with or without associated infection) of approximately 1.1 per thousand patients exposed, with a very wide 95% confidence interval, i.e., 2.2 cases per 10,000 to 3.1 cases per 1000. If a patient develops a sore throat, fever, stomatitis, or other signs of infection, along with a low WBC count, treatment with REMERON should be discontinued and the patient should be closely monitored.

MAO Inhibitors

In patients receiving other drugs for major depressive disorder in combination with a monoamine oxidase inhibitor (MAOI) and in patients who have recently discontinued a drug for major depressive disorder and then are started on an MAOI, there have been reports of serious and sometimes fatal reactions, including nausea, vomiting, flushing, dizziness, tremor, myoclonus, rigidity, diaphoresis, hyperthermia, autonomic instability with rapid fluctuations of vital signs, seizures, and mental status changes ranging from agitation to coma. Although there are no human data pertinent to such an interaction with REMERON (mirtazapine) Tablets, it is recommended that REMERON not be used in combination with an MAOI, or within 14 days of initiating or discontinuing therapy with an MAOI.

Serotonin Syndrome or Neuroleptic Malignant Syndrome (NMS)-like Reactions

The development of a potentially life-threatening serotonin syndrome or Neuroleptic Malignant Syndrome (NMS)-like reactions have been reported with SSRIs, SNRIs, MAOIs, and other serotonergic drugs used as monotherapy, including REMERON, but particularly with concomitant use of serotonergic drugs (including triptans) with drugs which impair metabolism of serotonin (including MAOIs), or with antipsychotics or other dopamine antagonists. Serotonin syndrome symptoms may include mental status changes (e.g., agitation, hallucinations, coma), autonomic instability (e.g., tachycardia, labile blood pressure, hyperthermia), neuromuscular aberrations (e.g., hyperreflexia, incoordination) and/or gastrointestinal symptoms (e.g., nausea, vomiting, diarrhea). Serotonin syndrome, in its most severe form can resemble neuroleptic malignant syndrome, which includes hyperthermia, muscle rigidity, autonomic instability with possible rapid fluctuation of vital signs, and mental status changes. Patients should be monitored for the emergence of serotonin syndrome or NMS-like signs and symptoms.

The concomitant use of REMERON with MAOIs intended to treat depression is contraindicated [see CONTRAINDICATIONS].

If concomitant treatment of REMERON with a 5-hydroxytryptamine receptor agonist (triptan) is clinically warranted, careful observation of the patient is advised, particularly during treatment initiation and dose increases.

The concomitant use of REMERON with serotonin precursors (such as tryptophan) is not recommended.

Treatment with REMERON and any concomitant serotonergic or antidopaminergic agents, including antipsychotics, should be discontinued immediately if the above events occur and supportive symptomatic treatment should be initiated.

PRECAUTIONS

General

Discontinuation Symptoms

There have been reports of adverse reactions upon the discontinuation of REMERON® (mirtazapine) Tablets (particularly when abrupt), including but not limited to the following: dizziness, abnormal dreams, sensory disturbances (including paresthesia and electric shock sensations), agitation, anxiety, fatigue, confusion, headache, tremor, nausea, vomiting, and sweating, or other symptoms which may be of clinical significance. The majority of the reported cases are mild and self-limiting. Even though these have been reported as adverse reactions, it should be realized that these symptoms may be related to underlying disease.

Patients currently taking REMERON should NOT discontinue treatment abruptly, due to risk of discontinuation symptoms. At the time that a medical decision is made to discontinue treatment with REMERON, a gradual reduction in the dose, rather than an abrupt cessation, is recommended.

Akathisia/Psychomotor Restlessness

The use of antidepressants has been associated with the development of akathisia, characterized by a subjectively unpleasant or distressing restlessness and need to move, often accompanied by an inability to sit or stand still. This is most likely to occur within the first few weeks of treatment. In patients who develop these symptoms, increasing the dose may be detrimental.

Hyponatremia

Hyponatremia has been reported very rarely with the use of mirtazapine. Caution should be exercised in patients at risk, such as elderly patients or patients concomitantly treated with medications known to cause hyponatremia.

Somnolence

In US controlled studies, somnolence was reported in 54% of patients treated with REMERON (mirtazapine) Tablets, compared to 18% for placebo and 60% for amitriptyline. In these studies, somnolence resulted in discontinuation for 10.4% of REMERON-treated patients, compared to 2.2% for placebo. It is unclear whether or not tolerance develops to the somnolent effects of REMERON. Because of the potentially significant effects of REMERON on impairment of performance, patients should be cautioned about engaging in activities requiring alertness until they have been able to assess the drug's effect on their own psychomotor performance (see Information for Patients).

Dizziness

In US controlled studies, dizziness was reported in 7% of patients treated with REMERON, compared to 3% for placebo and 14% for amitriptyline. It is unclear whether or not tolerance develops to the dizziness observed in association with the use of REMERON.

Increased Appetite/Weight Gain

In US controlled studies, appetite increase was reported in 17% of patients treated with REMERON, compared to 2% for placebo and 6% for amitriptyline. In these same trials, weight gain of ≥7% of body weight was reported in 7.5% of patients treated with mirtazapine, compared to 0% for placebo and 5.9% for amitriptyline. In a pool of premarketing US studies, including many patients for long-term, open-label treatment, 8% of patients receiving REMERON discontinued for weight gain. In an 8-week-long pediatric clinical trial of doses between 15 to 45 mg/day, 49% of REMERON-treated patients had a weight gain of at least 7%, compared to 5.7% of placebo-treated patients (see PRECAUTIONS: Pediatric Use).

Cholesterol/Triglycerides

In US controlled studies, nonfasting cholesterol increases to ≥20% above the upper limits of normal were observed in 15% of patients treated with REMERON, compared to 7% for placebo and 8% for amitriptyline. In these same studies, nonfasting triglyceride increases to ≥500 mg/dL were observed in 6% of patients treated with mirtazapine, compared to 3% for placebo and 3% for amitriptyline.

Transaminase Elevations

Clinically significant ALT (SGPT) elevations (≥3 times the upper limit of the normal range) were observed in 2.0% (8/424) of patients exposed to REMERON in a pool of short-term US controlled trials, compared to 0.3% (1/328) of placebo patients and 2.0% (3/181) of amitriptyline patients. Most of these patients with ALT increases did not develop signs or symptoms associated with compromised liver function. While some patients were discontinued for the ALT increases, in other cases, the enzyme levels returned to normal despite continued REMERON treatment. REMERON should be used with caution in patients with impaired hepatic function (see CLINICAL PHARMACOLOGY and DOSAGE AND ADMINISTRATION).

Activation of Mania/Hypomania

Mania/hypomania occurred in approximately 0.2% (3/1299 patients) of REMERON-treated patients in US studies. Although the incidence of mania/hypomania was very low during treatment with mirtazapine, it should be used carefully in patients with a history of mania/hypomania.

Seizure

In premarketing clinical trials, only 1 seizure was reported among the 2796 US and non-US patients treated with REMERON. However, no controlled studies have been carried out in patients with a history of seizures. Therefore, care should be exercised when mirtazapine is used in these patients.

Use in Patients with Concomitant Illness

Clinical experience with REMERON in patients with concomitant systemic illness is limited. Accordingly, care is advisable in prescribing mirtazapine for patients with diseases or conditions that affect metabolism or hemodynamic responses.

REMERON has not been systematically evaluated or used to any appreciable extent in patients with a recent history of myocardial infarction or other significant heart disease. REMERON was associated with significant orthostatic hypotension in early clinical pharmacology trials with normal volunteers. Orthostatic hypotension was infrequently observed in clinical trials with depressed patients. REMERON should be used with caution in patients with known cardiovascular or cerebrovascular disease that could be exacerbated by hypotension (history of myocardial infarction, angina, or ischemic stroke) and conditions that would predispose patients to hypotension (dehydration, hypovolemia, and treatment with antihypertensive medication).

Mirtazapine clearance is decreased in patients with moderate [glomerular filtration rate (GFR) = 11–39 mL/min/1.73 m^2] and severe [GFR <10 mL/min/1.73 m^2] renal impairment, and also in patients with hepatic impairment. Caution is indicated in administering REMERON to such patients (see CLINICAL PHARMACOLOGY and DOSAGE AND ADMINISTRATION).

Information for Patients

Prescribers or other health professionals should inform patients, their families, and their caregivers about the benefits and risks associated with treatment with REMERON (mirtazapine) Tablets and should counsel them in its appropriate use. A patient Medication Guide about "Antidepressant Medicines, Depression and other Serious Mental Illnesses, and Suicidal Thoughts or Actions" is available for REMERON. The prescriber or health professional should instruct patients, their families, and their caregivers to read the Medication Guide and should assist them in understanding its contents. Patients should be given the opportunity to discuss the contents of the Medication Guide and to obtain answers to any questions they may have. The complete text of the Medication Guide is reprinted at the end of this document.

Patients should be advised of the following issues and asked to alert their prescriber if these occur while taking REMERON.

Clinical Worsening and Suicide Risk

Patients, their families, and their caregivers should be encouraged to be alert to the emergence of anxiety, agitation, panic attacks, insomnia, irritability, hostility, aggressiveness, impulsivity, akathisia (psychomotor restlessness), hypomania, mania, other unusual changes in behavior, worsening of depression, and suicidal ideation, especially early during antidepressant treatment and when the dose is adjusted up or down. Families and caregivers of patients should be advised to look for the emergence of such symptoms on a day-to-day basis, since changes may be abrupt. Such symptoms should be reported to the patient's prescriber or health professional, especially if they are severe, abrupt in onset, or were not part of the patient's presenting symptoms. Symptoms such as these may be associated with an increased risk for suicidal thinking and behavior and indicate a need for very close monitoring and possibly changes in the medication.

Agranulocytosis

Patients who are to receive REMERON should be warned about the risk of developing agranulocytosis. Patients should be advised to contact their physician if they experience any indication of infection such as fever, chills, sore throat, mucous membrane ulceration, or other possible signs of infection. Particular attention should be paid to any flu-like complaints or other symptoms that might suggest infection.

Interference with Cognitive and Motor Performance

REMERON may impair judgment, thinking, and particularly, motor skills, because of its prominent sedative effect. The drowsiness associated with mirtazapine use may impair a patient's ability to drive, use machines, or perform tasks that require alertness. Thus, patients should be cautioned about engaging in hazardous activities until they are reasonably certain that REMERON therapy does not adversely affect their ability to engage in such activities.

Completing Course of Therapy

While patients may notice improvement with REMERON therapy in 1 to 4 weeks, they should be advised to continue therapy as directed.

Concomitant Medication

Patients should be advised to inform their physician if they are taking, or intend to take, any prescription or over-the-counter drugs, since there is a potential for REMERON to interact with other drugs.

Alcohol

The impairment of cognitive and motor skills produced by REMERON has been shown to be additive with those produced by alcohol. Accordingly, patients should be advised to avoid alcohol while taking mirtazapine.

Pregnancy

Patients should be advised to notify their physician if they become pregnant or intend to become pregnant during REMERON therapy.

Nursing

Patients should be advised to notify their physician if they are breast-feeding an infant.

Laboratory Tests

There are no routine laboratory tests recommended.

Drug Interactions

As with other drugs, the potential for interaction by a variety of mechanisms (e.g., pharmacodynamic, pharmacokinetic inhibition or enhancement, etc.) is a possibility (see CLINICAL PHARMACOLOGY).

Monoamine Oxidase Inhibitors

(See CONTRAINDICATIONS, WARNINGS, and DOSAGE AND ADMINISTRATION.)

Serotonergic drugs

Based on the mechanism of action of mirtazapine and the potential for serotonin syndrome, caution is advised when REMERON Tablets are coadministered with other drugs or agents that may affect the serotonergic neurotransmitter systems, such as tryptophan, triptans, linezolid, serotonin reuptake inhibitors, venlafaxine, lithium, tramadol, or St. John's wort (see CONTRAINDICATIONS and WARNINGS).

Drugs Affecting Hepatic Metabolism

The metabolism and pharmacokinetics of REMERON (mirtazapine) Tablets may be affected by the induction or inhibition of drug-metabolizing enzymes.

Drugs that are Metabolized by and/or Inhibit Cytochrome P450 Enzymes

CYP Enzyme Inducers (these studies used both drugs at steady state)

Phenytoin

In healthy male patients (n=18), phenytoin (200 mg daily) increased mirtazapine (30 mg daily) clearance about 2-fold, resulting in a decrease in average plasma mirtazapine concentrations of 45%. Mirtazapine did not significantly affect the pharmacokinetics of phenytoin.

Carbamazepine

In healthy male patients (n=24), carbamazepine (400 mg b.i.d.) increased mirtazapine (15 mg b.i.d.) clearance about 2-fold, resulting in a decrease in average plasma mirtazapine concentrations of 60%.

When phenytoin, carbamazepine, or another inducer of hepatic metabolism (such as rifampicin) is added to mirtazapine therapy, the mirtazapine dose may have to be increased. If treatment with such a medicinal product is discontinued, it may be necessary to reduce the mirtazapine dose.

CYP Enzyme Inhibitors

Cimetidine

In healthy male patients (n=12), when cimetidine, a weak inhibitor of CYP1A2, CYP2D6, and CYP3A4, given at 800 mg b.i.d. at steady state was coadministered with mirtazapine (30 mg daily) at steady state, the Area Under the Curve (AUC) of mirtazapine increased more than 50%. Mirtazapine did not cause relevant changes in the pharmacokinetics of cimetidine. The mirtazapine dose may have to be decreased when concomitant treatment with cimetidine is started, or increased when cimetidine treatment is discontinued.

Ketoconazole

In healthy, male, Caucasian patients (n=24), coadministration of the potent CYP3A4 inhibitor ketoconazole (200 mg b.i.d. for 6.5 days) increased the peak plasma levels and the AUC of a single 30-mg dose of mirtazapine by approximately 40% and 50%, respectively.

Caution should be exercised when coadministering mirtazapine with potent CYP3A4 inhibitors, HIV protease inhibitors, azole antifungals, erythromycin, or nefazodone.

Paroxetine

In an in vivo interaction study in healthy, CYP2D6 extensive metabolizer patients (n=24), mirtazapine (30 mg/day), at steady state, did not cause relevant changes in the pharmacokinetics of steady state paroxetine (40 mg/day), a CYP2D6 inhibitor.

Other Drug-Drug Interactions

Amitriptyline

In healthy, CYP2D6 extensive metabolizer patients (n=32), amitriptyline (75 mg daily), at steady state, did not cause relevant changes in the pharmacokinetics of steady state mirtazapine (30 mg daily); mirtazapine also did not cause relevant changes to the pharmacokinetics of amitriptyline.

Warfarin

In healthy male subjects (n=16), mirtazapine (30 mg daily), at steady state, caused a small (0.2) but statistically significant increase in the International Normalized Ratio (INR) in subjects treated with warfarin. As at a higher dose of mirtazapine, a more pronounced effect can not be excluded. It is advisable to monitor the INR in case of concomitant treatment of warfarin with mirtazapine.

Lithium

No relevant clinical effects or significant changes in pharmacokinetics have been observed in healthy male subjects on concurrent treatment with subtherapeutic levels of lithium (600 mg/day for 10 days) at steady state and a single 30 mg dose of mirtazapine. The effects of higher doses of lithium on the pharmacokinetics of mirtazapine are unknown.

Risperidone

In an in vivo, nonrandomized, interaction study, subjects (n=6) in need of treatment with an antipsychotic and antidepressant drug, showed that mirtazapine (30 mg daily) at steady state did not influence the pharmacokinetics of risperidone (up to 3 mg b.i.d.).

Alcohol

Concomitant administration of alcohol (equivalent to 60 g) had a minimal effect on plasma levels of mirtazapine (15 mg) in 6 healthy male subjects. However, the impairment of cognitive and motor skills produced by REMERON were shown to be additive with those produced by alcohol. Accordingly, patients should be advised to avoid alcohol while taking REMERON.

Diazepam

Concomitant administration of diazepam (15 mg) had a minimal effect on plasma levels of mirtazapine (15 mg) in 12 healthy subjects. However, the impairment of motor skills produced by REMERON has been shown to be additive with those caused by diazepam. Accordingly, patients should be advised to avoid diazepam and other similar drugs while taking REMERON.

Carcinogenesis, Mutagenesis, Impairment of Fertility

Carcinogenesis

Carcinogenicity studies were conducted with mirtazapine given in the diet at doses of 2, 20, and 200 mg/kg/day to mice and 2, 20, and 60 mg/kg/day to rats. The highest doses used are approximately 20 and 12 times the maximum recommended human dose (MRHD) of 45 mg/day on an mg/m^2 basis in mice and rats, respectively. There was an increased incidence of hepatocellular adenoma and carcinoma in male mice at the high dose. In rats, there was an increase in hepatocellular adenoma in females at the mid and high doses and in hepatocellular tumors and thyroid follicular adenoma/cystadenoma and carcinoma in males at the high dose. The data suggest that the above effects could possibly be mediated by non-genotoxic mechanisms, the relevance of which to humans is not known.

The doses used in the mouse study may not have been high enough to fully characterize the carcinogenic potential of REMERON (mirtazapine) Tablets.

Mutagenesis

Mirtazapine was not mutagenic or clastogenic and did not induce general DNA damage as determined in several genotoxicity tests: Ames test, in vitro gene mutation assay in Chinese hamster V 79 cells, in vitro sister chromatid exchange assay in cultured rabbit lymphocytes, in vivo bone marrow micronucleus test in rats, and unscheduled DNA synthesis assay in HeLa cells.

Impairment of Fertility

In a fertility study in rats, mirtazapine was given at doses up to 100 mg/kg [20 times the maximum recommended human dose (MRHD) on an mg/m^2 basis]. Mating and conception were not affected by the drug, but estrous cycling was disrupted at doses that were 3 or more times the MRHD, and pre-implantation losses occurred at 20 times the MRHD.

Pregnancy

Teratogenic Effects – Pregnancy Category C

Reproduction studies in pregnant rats and rabbits at doses up to 100 mg/kg and 40 mg/kg, respectively [20 and 17 times the maximum recommended human dose (MRHD) on an mg/m^2 basis, respectively], have revealed no evidence of teratogenic effects. However, in rats, there was an increase in postimplantation losses in dams treated with mirtazapine. There was an increase in pup deaths during the first 3 days of lactation and a decrease in pup birth weights. The cause of these deaths is not known. The effects occurred at doses that were 20 times the MRHD, but not at 3 times the MRHD, on an mg/m^2 basis. There are no adequate and well-controlled studies in pregnant women. Because animal reproduction studies are not always predictive of human response, this drug should be used during pregnancy only if clearly needed.

Nursing Mothers

Because some REMERON may be excreted into breast milk, caution should be exercised when REMERON (mirtazapine) Tablets are administered to nursing women.

Pediatric Use

Safety and effectiveness in the pediatric population have not been established (see BOXED WARNING and WARNINGS: Clinical Worsening and Suicide Risk). Two placebo-controlled trials in 258 pediatric patients with MDD have been conducted with REMERON (mirtazapine) Tablets, and the data were not sufficient to support a claim for use in pediatric patients. Anyone considering the use of REMERON in a child or adolescent must balance the potential risks with the clinical need.

In an 8-week-long pediatric clinical trial of doses between 15 to 45 mg/day, 49% of REMERON-treated patients had a weight gain of at least 7%, compared to 5.7% of placebo-treated patients. The mean increase in weight was 4 kg (2 kg SD) for REMERON-treated patients versus 1 kg (2 kg SD) for placebo-treated patients (see PRECAUTIONS: Increased Appetite/Weight Gain).

Geriatric Use

Approximately 190 elderly individuals (≥65 years of age) participated in clinical studies with REMERON (mirtazapine) Tablets. This drug is known to be substantially excreted by the kidney (75%), and the risk of decreased clearance of this drug is greater in patients with impaired renal function. Because elderly patients are more likely to have decreased renal function, care should be taken in dose selection. Sedating drugs may cause confusion and over-sedation in the elderly. No unusual adverse age-related phenomena were identified in this group. Pharmacokinetic studies revealed a decreased clearance in the elderly. Caution is indicated in administering REMERON to elderly patients (see CLINICAL PHARMACOLOGY and DOSAGE AND ADMINISTRATION).

ADVERSE REACTIONS

Associated with Discontinuation of Treatment

Approximately 16% of the 453 patients who received REMERON® (mirtazapine) Tablets in US 6-week controlled clinical trials discontinued treatment due to an adverse experience, compared to 7% of the 361 placebo-treated patients in those studies. The most common events (≥1%) associated with discontinuation and considered to be drug related (i.e., those events associated with dropout at a rate at least twice that of placebo) are included in Table 2.

Table 2: Common Adverse Events Associated with Discontinuation of Treatment in 6-Week US REMERON Trials
Adverse Event | Percentage of Patients Discontinuing with Adverse Event
Adverse Event | REMERON (n=453) | Placebo (n=361)
Somnolence | 10.4% | 2.2%
Nausea | 1.5% | 0%

Commonly Observed Adverse Events in US Controlled Clinical Trials

The most commonly observed adverse events associated with the use of REMERON (mirtazapine) Tablets (incidence of 5% or greater) and not observed at an equivalent incidence among placebo-treated patients (REMERON incidence at least twice that for placebo) are listed in Table 3.

Table 3: Common Treatment-Emergent Adverse Events Associated with the Use of REMERON in 6-Week US Trials
Adverse Event | Percentage of Patients Reporting Adverse Event
Adverse Event | REMERON (n=453) | Placebo (n=361)
Somnolence | 54% | 18%
Increased Appetite | 17% | 2%
Weight Gain | 12% | 2%
Dizziness | 7% | 3%

Adverse Events Occurring at an Incidence of 1% or More Among REMERON-Treated Patients

Table 4 enumerates adverse events that occurred at an incidence of 1% or more, and were more frequent than in the placebo group, among REMERON (mirtazapine) Tablets-treated patients who participated in short-term US placebo-controlled trials in which patients were dosed in a range of 5 to 60 mg/day. This table shows the percentage of patients in each group who had at least 1 episode of an event at some time during their treatment. Reported adverse events were classified using a standard COSTART-based dictionary terminology.

The prescriber should be aware that these figures cannot be used to predict the incidence of side effects in the course of usual medical practice where patient characteristics and other factors differ from those which prevailed in the clinical trials. Similarly, the cited frequencies cannot be compared with figures obtained from other investigations involving different treatments, uses, and investigators. The cited figures, however, do provide the prescribing physician with some basis for estimating the relative contribution of drug and nondrug factors to the side-effect incidence rate in the population studied.

Table 4: Incidence of Adverse Clinical Experiences [Events reported by at least 1% of patients treated with REMERON are included, except the following events which had an incidence on placebo greater than or equal to REMERON: headache, infection, pain, chest pain, palpitation, tachycardia, postural hypotension, nausea, dyspepsia, diarrhea, flatulence, insomnia, nervousness, libido decreased, hypertonia, pharyngitis, rhinitis, sweating, amblyopia, tinnitus, taste perversion.] (≥1%) in Short-Term US Controlled Studies
Body System Adverse Clinical Experience | REMERON (n=453) | Placebo (n=361)
Body as a Whole
Asthenia | 8% | 5%
Flu Syndrome | 5% | 3%
Back Pain | 2% | 1%
Digestive System
Dry Mouth | 25% | 15%
Increased Appetite | 17% | 2%
Constipation | 13% | 7%
Metabolic and Nutritional Disorders
Weight Gain | 12% | 2%
Peripheral Edema | 2% | 1%
Edema | 1% | 0%
Musculoskeletal System
Myalgia | 2% | 1%
Nervous System
Somnolence | 54% | 18%
Dizziness | 7% | 3%
Abnormal Dreams | 4% | 1%
Thinking Abnormal | 3% | 1%
Tremor | 2% | 1%
Confusion | 2% | 0%
Respiratory System
Dyspnea | 1% | 0%
Urogenital System
Urinary Frequency | 2% | 1%

ECG Changes

The electrocardiograms for 338 patients who received REMERON (mirtazapine) Tablets and 261 patients who received placebo in 6-week, placebo-controlled trials were analyzed. Prolongation in QTc ≥500 msec was not observed among mirtazapine-treated patients; mean change in QTc was +1.6 msec for mirtazapine and –3.1 msec for placebo. Mirtazapine was associated with a mean increase in heart rate of 3.4 bpm, compared to 0.8 bpm for placebo. The clinical significance of these changes is unknown.

Other Adverse Events Observed During the Premarketing Evaluation of REMERON

During its premarketing assessment, multiple doses of REMERON (mirtazapine) Tablets were administered to 2796 patients in clinical studies. The conditions and duration of exposure to mirtazapine varied greatly, and included (in overlapping categories) open and double-blind studies, uncontrolled and controlled studies, inpatient and outpatient studies, fixed-dose and titration studies. Untoward events associated with this exposure were recorded by clinical investigators using terminology of their own choosing. Consequently, it is not possible to provide a meaningful estimate of the proportion of individuals experiencing adverse events without first grouping similar types of untoward events into a smaller number of standardized event categories.

In the tabulations that follow, reported adverse events were classified using a standard COSTART-based dictionary terminology. The frequencies presented, therefore, represent the proportion of the 2796 patients exposed to multiple doses of REMERON who experienced an event of the type cited on at least 1 occasion while receiving REMERON. All reported events are included except those already listed in Table 4, those adverse experiences subsumed under COSTART terms that are either overly general or excessively specific so as to be uninformative, and those events for which a drug cause was very remote.

It is important to emphasize that, although the events reported occurred during treatment with REMERON, they were not necessarily caused by it.

Events are further categorized by body system and listed in order of decreasing frequency according to the following definitions: frequent adverse events are those occurring on 1 or more occasions in at least 1/100 patients; infrequent adverse events are those occurring in 1/100 to 1/1000 patients; rare events are those occurring in fewer than 1/1000 patients. Only those events not already listed in Table 4 appear in this listing. Events of major clinical importance are also described in the WARNINGS and PRECAUTIONS sections.

Body as a Whole: frequent: malaise, abdominal pain, abdominal syndrome acute; infrequent: chills, fever, face edema, ulcer, photosensitivity reaction, neck rigidity, neck pain, abdomen enlarged; rare: cellulitis, chest pain substernal.

Cardiovascular System: frequent: hypertension, vasodilatation; infrequent: angina pectoris, myocardial infarction, bradycardia, ventricular extrasystoles, syncope, migraine, hypotension; rare: atrial arrhythmia, bigeminy, vascular headache, pulmonary embolus, cerebral ischemia, cardiomegaly, phlebitis, left heart failure.

Digestive System: frequent: vomiting, anorexia; infrequent: eructation, glossitis, cholecystitis, nausea and vomiting, gum hemorrhage, stomatitis, colitis, liver function tests abnormal; rare: tongue discoloration, ulcerative stomatitis, salivary gland enlargement, increased salivation, intestinal obstruction, pancreatitis, aphthous stomatitis, cirrhosis of liver, gastritis, gastroenteritis, oral moniliasis, tongue edema.

Endocrine System: rare: goiter, hypothyroidism.

Hemic and Lymphatic System: rare: lymphadenopathy, leukopenia, petechia, anemia, thrombocytopenia, lymphocytosis, pancytopenia.

Metabolic and Nutritional Disorders: frequent: thirst; infrequent: dehydration, weight loss; rare: gout, SGOT increased, healing abnormal, acid phosphatase increased, SGPT increased, diabetes mellitus, hyponatremia.

Musculoskeletal System: frequent: myasthenia, arthralgia; infrequent: arthritis, tenosynovitis; rare: pathologic fracture, osteoporosis fracture, bone pain, myositis, tendon rupture, arthrosis, bursitis.

Nervous System: frequent: hypesthesia, apathy, depression, hypokinesia, vertigo, twitching, agitation, anxiety, amnesia, hyperkinesia, paresthesia; infrequent: ataxia, delirium, delusions, depersonalization, dyskinesia, extrapyramidal syndrome, libido increased, coordination abnormal, dysarthria, hallucinations, manic reaction, neurosis, dystonia, hostility, reflexes increased, emotional lability, euphoria, paranoid reaction; rare: aphasia, nystagmus, akathisia (psychomotor restlessness), stupor, dementia, diplopia, drug dependence, paralysis, grand mal convulsion, hypotonia, myoclonus, psychotic depression, withdrawal syndrome, serotonin syndrome.

Respiratory System: frequent: cough increased, sinusitis; infrequent: epistaxis, bronchitis, asthma, pneumonia; rare: asphyxia, laryngitis, pneumothorax, hiccup.

Skin and Appendages: frequent: pruritus, rash; infrequent: acne, exfoliative dermatitis, dry skin, herpes simplex, alopecia; rare: urticaria, herpes zoster, skin hypertrophy, seborrhea, skin ulcer.

Special Senses: infrequent: eye pain, abnormality of accommodation, conjunctivitis, deafness, keratoconjunctivitis, lacrimation disorder, glaucoma, hyperacusis, ear pain; rare: blepharitis, partial transitory deafness, otitis media, taste loss, parosmia.

Urogenital System: frequent: urinary tract infection; infrequent: kidney calculus, cystitis, dysuria, urinary incontinence, urinary retention, vaginitis, hematuria, breast pain, amenorrhea, dysmenorrhea, leukorrhea, impotence; rare: polyuria, urethritis, metrorrhagia, menorrhagia, abnormal ejaculation, breast engorgement, breast enlargement, urinary urgency.

Other Adverse Events Observed During Postmarketing Evaluation of REMERON

Adverse events reported since market introduction, which were temporally (but not necessarily causally) related to mirtazapine therapy, include 4 cases of the ventricular arrhythmia torsades de pointes. In 3 of the 4 cases, however, concomitant drugs were implicated. All patients recovered.

Cases of severe skin reactions, including Stevens-Johnson Syndrome, bullous dermatitis, erythema multiforme and toxic epidermal necrolysis have also been reported.

DRUG ABUSE AND DEPENDENCE

Controlled Substance Class

REMERON® (mirtazapine) Tablets are not a controlled substance.

Physical and Psychologic Dependence

REMERON (mirtazapine) Tablets have not been systematically studied in animals or humans for its potential for abuse, tolerance, or physical dependence. While the clinical trials did not reveal any tendency for any drug-seeking behavior, these observations were not systematic and it is not possible to predict on the basis of this limited experience the extent to which a CNS-active drug will be misused, diverted and/or abused once marketed. Consequently, patients should be evaluated carefully for history of drug abuse, and such patients should be observed closely for signs of REMERON misuse or abuse (e.g., development of tolerance, incrementations of dose, drug-seeking behavior).

OVERDOSAGE

Human Experience

There is very limited experience with REMERON® (mirtazapine) Tablets overdose. In premarketing clinical studies, there were 8 reports of REMERON overdose alone or in combination with other pharmacological agents. The only drug overdose death reported while taking REMERON was in combination with amitriptyline and chlorprothixene in a non-US clinical study. Based on plasma levels, the REMERON dose taken was 30 to 45 mg, while plasma levels of amitriptyline and chlorprothixene were found to be at toxic levels. All other premarketing overdose cases resulted in full recovery. Signs and symptoms reported in association with overdose included disorientation, drowsiness, impaired memory, and tachycardia. There were no reports of ECG abnormalities, coma, or convulsions following overdose with REMERON alone.

Overdose Management

Treatment should consist of those general measures employed in the management of overdose with any drug effective in the treatment of major depressive disorder. Ensure an adequate airway, oxygenation, and ventilation. Monitor cardiac rhythm and vital signs. General supportive and symptomatic measures are also recommended. Induction of emesis is not recommended. Gastric lavage with a large-bore orogastric tube with appropriate airway protection, if needed, may be indicated if performed soon after ingestion, or in symptomatic patients.

Activated charcoal should be administered. There is no experience with the use of forced diuresis, dialysis, hemoperfusion, or exchange transfusion in the treatment of mirtazapine overdosage. No specific antidotes for mirtazapine are known.

In managing overdosage, consider the possibility of multiple-drug involvement. The physician should consider contacting a poison control center for additional information on the treatment of any overdose. Telephone numbers for certified poison control centers are listed in the Physicians' Desk Reference (PDR).

DOSAGE AND ADMINISTRATION

Initial Treatment

The recommended starting dose for REMERON® (mirtazapine) Tablets is 15 mg/day, administered in a single dose, preferably in the evening prior to sleep. In the controlled clinical trials establishing the efficacy of REMERON in the treatment of major depressive disorder, the effective dose range was generally 15 to 45 mg/day. While the relationship between dose and satisfactory response in the treatment of major depressive disorder for REMERON has not been adequately explored, patients not responding to the initial 15-mg dose may benefit from dose increases up to a maximum of 45 mg/day. REMERON has an elimination half-life of approximately 20 to 40 hours; therefore, dose changes should not be made at intervals of less than 1 to 2 weeks in order to allow sufficient time for evaluation of the therapeutic response to a given dose.

Elderly and Patients with Renal or Hepatic Impairment

The clearance of mirtazapine is reduced in elderly patients and in patients with moderate to severe renal or hepatic impairment. Consequently, the prescriber should be aware that plasma mirtazapine levels may be increased in these patient groups, compared to levels observed in younger adults without renal or hepatic impairment (see PRECAUTIONS and CLINICAL PHARMACOLOGY).

Maintenance/Extended Treatment

It is generally agreed that acute episodes of depression require several months or longer of sustained pharmacological therapy beyond response to the acute episode. Systematic evaluation of REMERON (mirtazapine) Tablets has demonstrated that its efficacy in major depressive disorder is maintained for periods of up to 40 weeks following 8 to 12 weeks of initial treatment at a dose of 15 to 45 mg/day (see CLINICAL PHARMACOLOGY). Based on these limited data, it is unknown whether or not the dose of REMERON needed for maintenance treatment is identical to the dose needed to achieve an initial response. Patients should be periodically reassessed to determine the need for maintenance treatment and the appropriate dose for such treatment.

Switching Patients To or From a Monoamine Oxidase Inhibitor

Concomitant use of REMERON (mirtazapine) Tablets with MAOIs is contraindicated. At least 14 days should elapse between discontinuation of an MAOI and initiation of therapy with REMERON (mirtazapine) Tablets. In addition, at least 14 days should be allowed after stopping REMERON before starting an MAOI.

Discontinuation of Remeron Treatment

Symptoms associated with the discontinuation or dose reduction of REMERON Tablets have been reported. Patients should be monitored for these and other symptoms when discontinuing treatment or during dosage reduction. A gradual reduction in the dose over several weeks, rather than abrupt cessation, is recommended whenever possible. If intolerable symptoms occur following a decrease in the dose or upon discontinuation of treatment, dose titration should be managed on the basis of the patient's clinical response (see PRECAUTIONS and ADVERSE REACTIONS).

HOW SUPPLIED

REMERON® (mirtazapine) Tablets are supplied as:

15 mg Tablets — oval, scored, yellow, coated, with "Organon" debossed on 1 side and "T3Z" on the other side.

 | Bottles of 30 | NDC 54868-4848-0

Storage

Store at 25°C (77°F); excursions permitted to 15°–30°C (59°–86°F) [see USP Controlled Room Temperature]. Protect from light and moisture.

Rx only

Manufactured by: N.V. Organon, Oss, The Netherlands, a subsidiary of
MERCK & CO., INC.
Whitehouse Station, NJ 08889, USA

Distributed by: Schering Corporation, a subsidiary of
MERCK & CO., INC.
Whitehouse Station, NJ 08889, USA.

Copyright © 1996, 2010 N.V. Organon, a subsidiary of Merck & Co., Inc.
All rights reserved.

Rev. 12/11
900246-MRZ-TB-USPI.5

Additional barcode labeling by:
Physicians Total Care, Inc.
Tulsa, Oklahoma 74146

Medication Guide

REMERON® (rĕm' - ĕ – rŏn)
(mirtazapine)
Tablets

Read the Medication Guide that comes with REMERON before you start taking it and each time you get a refill. There may be new information. This Medication Guide does not take the place of talking to your healthcare provider about your medical condition or treatment. If you have any questions about REMERON, talk to your healthcare provider.

What is the most important information I should know about REMERON®?

REMERON and other antidepressant medicines may cause serious side effects, including:

1. Suicidal thoughts or actions:

- REMERON and other antidepressant medicines may increase suicidal thoughts or actions in some children, teenagers, or young adults within the first few months of treatment or when the dose is changed.
- Depression or other serious mental illnesses are the most important causes of suicidal thoughts or actions.
- Watch for these changes and call your healthcare provider right away if you notice:

  - New or sudden changes in mood, behavior, actions, thoughts, or feelings, especially if severe.
  - Pay particular attention to such changes when REMERON is started or when the dose is changed.

Keep all follow-up visits with your healthcare provider and call between visits if you are worried about symptoms.

Call your healthcare provider right away if you have any of the following symptoms, or call 911 if an emergency, especially if they are new, worse, or worry you:

  - attempts to commit suicide
  - acting on dangerous impulses
  - acting aggressive or violent
  - thoughts about suicide or dying
  - new or worse depression
  - new or worse anxiety or panic attacks
  - feeling agitated, restless, angry or irritable
  - trouble sleeping
  - an increase in activity or talking more than what is normal for you
  - other unusual changes in behavior or mood

Call your healthcare provider right away if you have any of the following symptoms, or call 911 if an emergency. REMERON may be associated with these serious side effects:

2. Manic episodes:

- greatly increased energy
- severe trouble sleeping
- racing thoughts
- reckless behavior
- unusually grand ideas
- excessive happiness or irritability
- talking more or faster than usual

3. Decreased White Blood Cells called neutrophils, which are needed to fight infections. Tell your doctor if you have any indication of infection such as fever, chills, sore throat, or mouth or nose sores, especially symptoms which are flu-like.

4. Serotonin Syndrome or Neuroleptic Malignant Syndrome-like reactions. This condition can be life-threatening and may include:

- agitation, hallucinations, coma or other changes in mental status
- coordination problems or muscle twitching (overactive reflexes)
- racing heartbeat, high or low blood pressure
- sweating or fever
- nausea, vomiting, or diarrhea
- muscle rigidity

5. Seizures

6. Low salt (sodium) levels in the blood.

Elderly people may be at greater risk for this. Symptoms may include:

- headache
- weakness or feeling unsteady
- confusion, problems concentrating or thinking or memory problems

7. Sleepiness. It is best to take REMERON® close to bedtime.

8. Severe skin reactions: Call your doctor right away if you have any or all of the following symptoms:

- severe rash with skin swelling (including on the palms of the hands and soles of the feet)
- painful reddening of the skin and/or blisters/ulcers on the body or in the mouth

9. Severe allergic reactions: trouble breathing, swelling of the face, tongue, eyes or mouth

- rash, itchy welts (hives) or blisters, alone or with fever or joint pain

10. Increases in appetite or weight. Children and adolescents should have height and weight monitored during treatment.

11. Increased cholesterol and triglyceride levels in your blood

Do not stop REMERON without first talking to your healthcare provider. Stopping REMERON too quickly may cause potentially serious symptoms including:

- dizziness
- abnormal dreams
- agitation
- anxiety
- fatigue
- confusion
- headache
- shaking
- tingling sensation
- nausea, vomiting
- sweating

What is REMERON®?

REMERON is a prescription medicine used to treat depression. It is important to talk with your healthcare provider about the risks of treating depression and also the risks of not treating it. You should discuss all treatment choices with your healthcare provider.

Talk to your healthcare provider if you do not think that your condition is getting better with REMERON treatment.

Who should not take REMERON®?

Do not take REMERON if you:

- are allergic to mirtazapine or any of the ingredients in REMERON. See the end of this Medication Guide for a complete list of ingredients in REMERON.
- take a Monoamine Oxidase Inhibitor (MAOI). Ask your healthcare provider or pharmacist if you are not sure if you take an MAOI, including the antibiotic linezolid.

  - it is recommended that REMERON not be used in combination with an MAOI within 14 days of initiating or discontinuing therapy with an MAOI.

People who take REMERON close in time to an MAOI may have serious or even life-threatening side effects. Get medical help right away if you have any of these symptoms:

  - high fever
  - uncontrolled muscle spasms
  - stiff muscles
  - rapid changes in heart rate or blood pressure
  - confusion
  - loss of consciousness (pass out)

What should I tell my healthcare provider before taking REMERON®? Ask if you are not sure.

Before starting REMERON, tell your healthcare provider if you:

- Are taking certain drugs such as:

  - Triptans used to treat migraine headache
  - Medicines used to treat mood, anxiety, psychotic or thought disorders, including tricyclics, lithium, SSRIs, SNRIs, or antipsychotics
  - Tramadol used to treat pain
  - Over-the-counter supplements such as tryptophan or St. John's Wort
  - Phenytoin, carbamazepine, or rifampicin (these drugs can decrease your blood level of REMERON)
  - Cimetidine or ketoconazole (these drugs can increase your blood level of REMERON)

- Have or had:

  - liver problems
  - kidney problems
  - heart problems
  - seizures or convulsions
  - bipolar disorder or mania
  - a tendency to get dizzy or faint

- are pregnant or plan to become pregnant. It is not known if REMERON will harm your unborn baby. Talk to your healthcare provider about the benefits and risks of treating depression during pregnancy
- are breast-feeding or plan to breast-feed. Some REMERON may pass into your breast milk. Talk to your healthcare provider about the best way to feed your baby while taking REMERON

Tell your healthcare provider about all the medicines that you take, including prescription and non-prescription medicines, vitamins, and herbal supplements. REMERON and some medicines may interact with each other, may not work as well, or may cause serious side effects.

Your healthcare provider or pharmacist can tell you if it is safe to take REMERON with your other medicines. Do not start or stop any medicine while taking REMERON without talking to your healthcare provider first.

BOXED WARNING

If you take REMERON, you should not take any other medicines that contain mirtazapine including REMERONSolTab.

How should I take REMERON®?

- Take REMERON exactly as prescribed. Your healthcare provider may need to change the dose of REMERON until it is the right dose for you.
- Take REMERON at the same time each day, preferably in the evening at bedtime.
- Swallow REMERON as directed.
- It is common for antidepressant medicines such as REMERON to take up to a few weeks before you start to feel better. Do not stop taking REMERON if you do not feel results right away.
- Do not stop taking or change the dose of REMERON without first talking to your doctor, even if you feel better.
- REMERON may be taken with or without food.
- If you miss a dose of REMERON, take the missed dose as soon as you remember. If it is almost time for the next dose, skip the missed dose and take your next dose at the regular time. Do not take two doses of REMERON at the same time.
- If you take too much REMERON, call your healthcare provider or poison control center right away, or get emergency treatment.

What should I avoid while taking REMERON®?

- REMERON can cause sleepiness or may affect your ability to make decisions, think clearly, or react quickly. You should not drive, operate heavy machinery, or do other dangerous activities until you know how REMERON affects you.
- Avoid drinking alcohol or taking diazepam (a medicine used for anxiety, insomnia and seizures, for example) or similar medicines while taking REMERON. If you are uncertain about whether certain medication can be taken with REMERON, please discuss with your doctor.

What are the possible side effects of REMERON®?

REMERON may cause serious side effects, including all of those described in the section entitled "What is the most important information I should know about REMERON®?"

Common possible side effects in people who take REMERON include:

- sleepiness
- increased appetite, weight gain
- dry mouth
- constipation
- dizziness
- abnormal dreams

Tell your healthcare provider if you have any side effect that bothers you or that does not go away. These are not all the possible side effects of REMERON. For more information, ask your healthcare provider or pharmacist.

CALL YOUR DOCTOR FOR MEDICAL ADVICE ABOUT SIDE EFFECTS. YOU MAY REPORT SIDE EFFECTS TO THE FDA AT 1-800-FDA-1088.

How should I store REMERON®?

- Store REMERON at room temperature 25°C (77°F). Storage at 15°C-30°C (59°F-86°F) is permitted occasionally.
- Keep REMERON away from light.
- Keep REMERON bottle closed tightly.

Keep REMERON and all medicines out of the reach of children.

General information about REMERON®

Medicines are sometimes prescribed for purposes other than those listed in a Medication Guide. Do not use REMERON for a condition for which it was not prescribed. Do not give REMERON to other people, even if they have the same condition. It may harm them.

This Medication Guide summarizes the most important information about REMERON. If you would like more information, talk with your healthcare provider. You may ask your healthcare provider or pharmacist for information about REMERON that is written for healthcare professionals.

For more information about REMERON call 1-800-526-4099 or go to www.REMERON.com.

What are the ingredients in REMERON®?

Active ingredient: mirtazapine

Inactive ingredients:

- 15mg tablets: Starch (corn), hydroxypropyl cellulose, magnesium stearate, colloidal silicon dioxide, lactose, hypromellose, polyethylene glycol 8000, titanium dioxide, ferric oxide (yellow).
- 30mg tablets: Starch (corn), hydroxypropyl cellulose, magnesium stearate, colloidal silicon dioxide, lactose, hypromellose, polyethylene glycol 8000, titanium dioxide, ferric oxide (yellow), ferric oxide (red).
- 45mg tablets: Starch (corn), hydroxypropyl cellulose, magnesium stearate, colloidal silicon dioxide, lactose, hypromellose, polyethylene glycol 8000, titanium dioxide.

This Medication Guide has been approved by the U.S. Food and Drug Administration.

Copyright © 2007, 2009 N.V. Organon, a subsidiary of Merck & Co., Inc.
All rights reserved.

Rev.12/11
900246-MRZ-TB-MG.5

Manufactured by: N.V. Organon, Oss, The Netherlands, a subsidiary of
MERCK & CO., INC.
Whitehouse Station, NJ 08889, USA

Distributed by: Schering Corporation, a subsidiary of
MERCK & CO., INC.
Whitehouse Station, NJ 08889, USA

PRINCIPAL DISPLAY PANEL - 15 mg Bottle Carton

NDC 54868-4848-0

30 Tablets

REMERON®
(mirtazapine)Tablets

Each tablet contains:

15 mg

Rx only